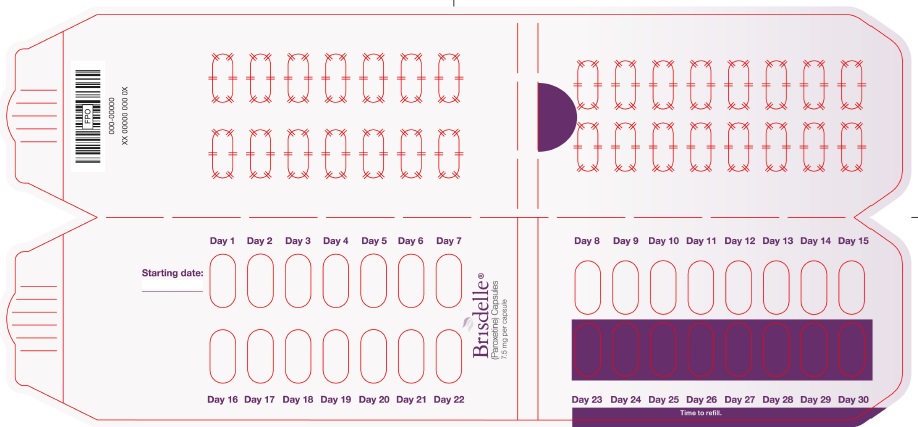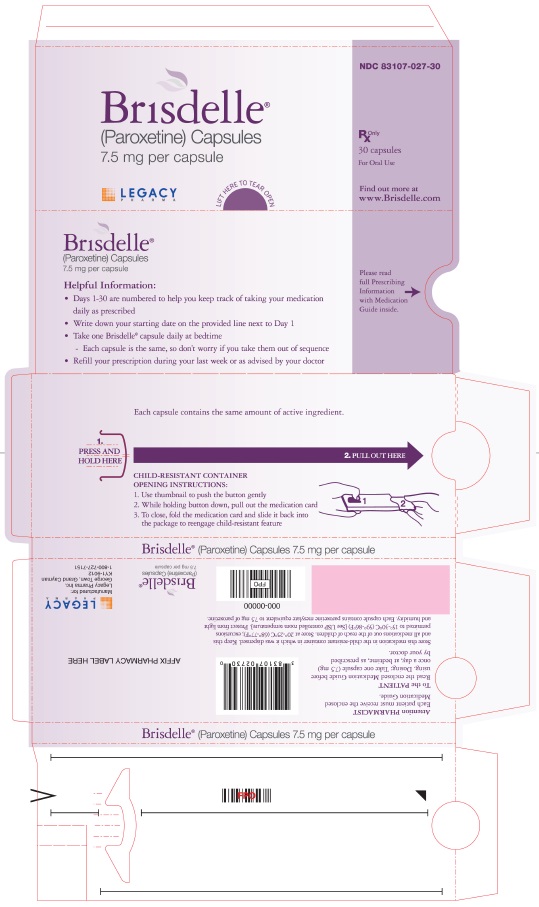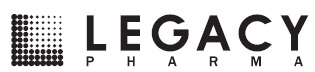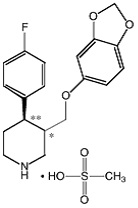 DRUG LABEL: BRISDELLE
NDC: 83107-027 | Form: CAPSULE
Manufacturer: Legacy Pharma USA, Inc.
Category: prescription | Type: HUMAN PRESCRIPTION DRUG LABEL
Date: 20250428

ACTIVE INGREDIENTS: PAROXETINE MESYLATE 7.5 mg/1 1
INACTIVE INGREDIENTS: CALCIUM PHOSPHATE, DIBASIC, ANHYDROUS; SODIUM STARCH GLYCOLATE TYPE A POTATO; MAGNESIUM STEARATE; GELATIN; TITANIUM DIOXIDE; FD&C YELLOW NO. 6; FD&C RED NO. 3; FD&C RED NO. 40; SHELLAC; FERROSOFERRIC OXIDE

HIGHLIGHTS OF PRESCRIBING INFORMATION

These highlights do not include all the information needed to use BRISDELLE safely and effectively. See full prescribing information for BRISDELLE.
BRISDELLE® (paroxetine) capsules, for oral use
Initial U.S. Approval: 1992

WARNING: SUICIDAL THOUGHTS AND BEHAVIORS

See full prescribing information for complete boxed warning.

Antidepressants, including selective serotonin reuptake inhibitors (SSRIs), increased the risk of suicidal thoughts and behavior in pediatric and young adult patients with major depressive disorder and other psychiatric disorder. Because BRISDELLE is an SSRI, closely monitor patients for clinical worsening and for emergence of suicidal thoughts and behaviors. BRISDELLE is not approved for use in pediatric and young adult patients (5.1).

1 INDICATIONS AND USAGE

BRISDELLE is a selective serotonin reuptake inhibitor (SSRI) indicated for the treatment of moderate to severe vasomotor symptoms associated with menopause (VMS) (1)

Limitations of Use: BRISDELLE is not indicated for the treatment of any psychiatric condition (1)

2 DOSAGE AND ADMINISTRATION

- The recommended dosage of BRISDELLE is 7.5 mg once daily, at bedtime (2.1)

3 DOSAGE FORMS AND STRENGTHS

Capsules: 7.5 mg (3)

4 CONTRAINDICATIONS

- Concurrent use with monoamine oxidase inhibitors (MAOI) or use within 14 days of MAOI use (2.2, 4.1, 5.2, 7.3)
- Use with thioridazine (4.2, 7.1)
- Use with pimozide (4.3, 7.1)
- Hypersensitivity to any ingredient in BRISDELLE (4.4)
- Pregnancy (4.5, 8.1)

5 WARNINGS AND PRECAUTIONS

- Suicidality: Monitor for suicidality or unusual changes in behavior (5.1)
- Serotonin Syndrome: BRISDELLE can cause serotonin syndrome with increased risk when co-administered with other serotonergic agents, but also when taken alone. If it occurs, discontinue BRISDELLE and serotonergic agents and initiate supportive measures (5.2, 7.3).
- Tamoxifen: Efficacy of tamoxifen may be reduced when administered concomitantly with BRISDELLE (5.3, 7.1)
- Abnormal Bleeding: Caution patients about the risk of bleeding associated with the concomitant use of BRISDELLE and non-steroidal anti-inflammatory drugs (NSAIDs), aspirin, or other drugs that affect coagulation (5.4, 7.1)
- Angle-Closure Glaucoma: Angle closure glaucoma has occurred in patients who have untreated anatomically narrow angles and who are treated with antidepressants. (5.5)
- Hyponatremia: Can occur in association with syndrome of inappropriate antidiuretic hormone secretion (SIADH) (5.6)
- Bone Fracture: Epidemiological studies have reported an association between SSRI treatment and fractures (5.7)
- Activation of Mania/Hypomania: Screen for bipolar disorder and monitor for mania/ hypomania (5.8)
- Seizures: Use cautiously in patients with a history of seizures or with conditions that potentially lower the seizure threshold (5.9)
- Sexual Dysfunction: BRISDELLE use may cause symptoms of sexual dysfunction. (5.12)

6 ADVERSE REACTIONS

The most common adverse reactions (≥ 2%) reported in clinical trials were: headache, fatigue, and nausea/vomiting (6.1)

To report SUSPECTED ADVERSE REACTIONS, contact Legacy Pharma Inc. at 1-800-727-7151 or FDA at 1-800-FDA-1088 or www.fda.gov/medwatch

7 DRUG INTERACTIONS

Paroxetine is a strong CYP2D6 inhibitor. Co-administration of BRISDELLE can alter concentrations of other drugs that are metabolized by CYP2D6. Consider potential drug interactions prior to and during therapy (5.3, 7.1, 7.3). See Full Prescribing Information for a list of clinically significant drug interactions (7.1, 7.2, 7.3)

FULL PRESCRIBING INFORMATION

WARNING: SUICIDAL THOUGHTS AND BEHAVIORS

Selective serotonin reuptake inhibitors (SSRIs) increased the risk of suicidal thoughts and behavior in pediatric and young adult patients in short-term trials for the treatment of major depressive disorder and other psychiatric disorders. Because BRISDELLE is an SSRI, closely monitor BRISDELLE-treated patients closely for emergence of suicidal thoughts and behaviors [see Warnings and Precautions (5.1)]. BRISDELLE is not approved for use in any psychiatric condition or in pediatric and young adult patients [see Indications and Usage (1) and Use in Specific Populations (8.4)].

1 INDICATIONS AND USAGE

BRISDELLE is indicated for the treatment of moderate to severe vasomotor symptoms (VMS) associated with menopause.

Limitations of Use:

BRISDELLE is not indicated for the treatment of any psychiatric condition. BRISDELLE has a lower recommended paroxetine dosage than that used to treat major depressive disorder, obsessive compulsive disorder, panic disorder, generalized anxiety disorder, social anxiety disorder, and post-traumatic stress disorder. The safety and effectiveness of the lower BRISDELLE dosage has not been established for any psychiatric condition. Patients who require paroxetine for treatment of a psychiatric condition should discontinue BRISDELLE and initiate a paroxetine-containing product that is indicated for such use.

2 DOSAGE AND ADMINISTRATION

2.1 Recommended Dosage

The recommended oral dosage of BRISDELLE for the treatment of moderate to severe VMS associated with menopause is 7.5 mg once daily, at bedtime, with or without food [see Clinical Pharmacology (12.3)].

2.2 Use of BRISDELLE Before or After a Monoamine Oxidase Inhibitor

Wait at least 14 days after discontinuation of a monoamine oxidase inhibitor (MAOI) before initiating therapy with BRISDELLE. Conversely, allow at least 14 days after stopping BRISDELLE before starting an MAOI [see Contraindications (4.1), Warnings and Precautions (5.2) and Drug Interactions (7.3)].

3 DOSAGE FORMS AND STRENGTHS

BRISDELLE is available as 7.5 mg pink capsules printed with black edible ink with “BRISDELLE” and “7.5 mg” on the capsule. Each capsule contains 9.69 mg of paroxetine mesylate equivalent to 7.5 mg paroxetine base.

4 CONTRAINDICATIONS

BRISDELLE is contraindicated in patients:

- Taking, or within 14 days of stopping, MAOIs (including the MAOIs linezolid and intravenous methylene blue) because of an increased risk of serotonin syndrome [see Warnings and Precautions (5.2), Drug Interaction (7)].
- Taking thioridazine because of risk of QT prolongation [see Warnings and Precautions (5.3), Drug Interaction (7)].
- Taking pimozide because of risk of QT prolongation [see Warnings and Precautions (5.3), Drug Interaction (7)].
- With known hypersensitivity (e.g., anaphylaxis, angioedema, Stevens-Johnson syndrome) to paroxetine or to any of the inactive ingredients in BRISDELLE [see Adverse Reactions (6.2)]
- Who are or become pregnant because menopausal VMS does not occur during pregnancy and BRISDELLE may cause fetal harm [see Use in Specific Populations (8.1)].

5 WARNINGS AND PRECAUTIONS

5.1 Suicidal Thoughts and Behaviors in Adolescents and Young Adults

SSRIs increased the risk of suicidal thoughts and behavior in pediatric and young adult patients in short-term trials for the treatment of major depressive disorder (MDD) and other psychiatric disorders - BRISDELLE is not approved for use in any psychiatric condition or in pediatric and young adult patients [see Indications and Usage (1) and Use in Specific Populations (8.4)]. There is limited information regarding suicidal thoughts and behaviors in females who use BRISDELLE for treatment of moderate to severe VMS associated with menopause. The BRISDELLE trials excluded females with a presence or history of previous psychiatric disorders.

Monitor all BRISDELLE-treated patients for any emergence of suicidal thoughts and behaviors, especially during the initial few months of BRISDELLE therapy. Counsel family members to monitor for changes in behavior and to alert the health care provider if such changes occur. Consider discontinuing BRISDELLE in patients who experience emergent suicidal thoughts or behaviors or symptoms that might be precursors to suicidal thoughts or behaviors, especially if these symptoms are severe, abrupt in onset, or were not part of the patient’s presenting symptoms.

5.2 Serotonin Syndrome

BRISDELLE can precipitate serotonin syndrome, a potentially life-threatening condition. The risk is increased with concomitant use of other serotonergic agents (including triptans, tricyclic antidepressants, fentanyl, tramadol, meperidine, methadone, lithium, tryptophan, buspirone, amphetamines, and St. John’s Wort) and with drugs that impair metabolism of serotonin, i.e., monoamine oxidase inhibitors (MAOIs) [see Contraindications (4), Drug Interactions (7.3)]. Serotonin syndrome can also occur when BRISDELLE is used alone.

Serotonin syndrome symptoms may include mental status changes (e.g., agitation, hallucinations, delirium, and coma), autonomic instability (e.g., tachycardia, labile blood pressure, dizziness, diaphoresis, flushing, hyperthermia), neuromuscular symptoms (e.g., tremor, rigidity, myoclonus, hyperreflexia, incoordination), and/or gastrointestinal symptoms (e.g., nausea, vomiting, diarrhea).

The concomitant use of BRISDELLE with MAOIs is contraindicated. Do not start BRISDELLE in a patient who is being treated with MAOIs such as linezolid or intravenous methylene blue. All reports with methylene blue that provided information on the route of administration involved intravenous administration in the dosage range of 1 mg/kg to 8 mg/kg. No reports involved the administration of methylene blue by other routes (such as oral or local tissue injection) or at lower dosages. If it is necessary to initiate treatment with an MAOI such as linezolid or intravenous methylene blue in a patient taking BRISDELLE, The patient should be taken off BRISDELLE before initiating treatment with the MAOI [see Contraindications (4.1)]. If concomitant use of BRISDELLE with other serotonergic drugs (besides MAOIs) is clinically warranted, consider the increased risk of serotonin syndrome and carefully observe the patient, particularly during BRISDELLE initiation [see Contraindications (4.1) Drug Interactions (7.3)].

Monitor all patients taking BRISDELLE for the emergence of serotonin syndrome. Discontinue BRISDELLE and any concomitant serotonergic agents immediately if the above events occur and initiate supportive symptomatic treatment.

5.3 Potential Impact on Tamoxifen Efficacy

Some studies have shown that the efficacy of tamoxifen, as measured by the risk of breast cancer relapse/mortality, may be reduced when concomitantly administered with paroxetine as a result of paroxetine’s irreversible inhibition of CYP2D6 and lower tamoxifen blood levels [see Drug Interactions (7.1)]. However, other studies have failed to demonstrate such a risk.

When tamoxifen is used for the treatment or prevention of breast cancer, weigh the likely benefit of BRISDELLE for treating moderate to severe VMS associated with menopause vs. the risk of possible decreased tamoxifen effectiveness, and consider avoiding the concomitant use of BRISDELLE.

5.4 Increased Risk of Bleeding

SSRIs, including BRISDELLE, increased the risk of bleeding events. Concomitant use of aspirin, nonsteroidal anti-inflammatory drugs (NSAIDs), other antiplatelet drugs, warfarin, and other anticoagulants may add to this risk [see Drug Interactions (7.3)]. Case reports and epidemiological studies (case-control and cohort design) have demonstrated an association between use of drugs that interfere with serotonin reuptake and the occurrence of gastrointestinal bleeding. Bleeding events related to SSRIs have ranged from ecchymosis, hematoma, epistaxis, and petechiae to life-threatening hemorrhages.

Inform patients about the risk of bleeding associated with the concomitant use of BRISDELLE and antiplatelet agents or anticoagulants [see Drug Interactions (7.1)]. For patients taking warfarin, carefully monitor the international normalized ratio.

5.5 Angle-Closure Glaucoma

The pupillary dilation that occurs following use of SSRIs, including BRISDELLE, may trigger an angle closure attack in a patient with anatomically narrow angles who does not have a patent iridectomy. Cases of angle-closure glaucoma associated with use of paroxetine have been reported. Avoid use of SSRIs, including BRISDELLE, in patients with untreated anatomically narrow angles.

5.6 Hyponatremia

Hyponatremia may occur as a result of treatment with SSRIs, including BRISDELLE. Cases with serum sodium lower than 110 mmol/L have been reported in patients using SSRIs. Geriatric patients, patients taking diuretics, and those who are volume-depleted may be at greater risk of developing hyponatremia with SSRIs [see Use in Specific Populations (8.5)]. Signs and symptoms of hyponatremia include headache, difficulty concentrating, memory impairment, confusion, weakness, and unsteadiness, which can lead to falls. Signs and symptoms associated with more severe and/or acute cases have included hallucination, syncope, seizure, coma, respiratory arrest, and death. In many cases, the hyponatremia appears to be the result of the syndrome of inappropriate antidiuretic hormone secretion (SIADH).

In patients with symptomatic hyponatremia, discontinue BRISDELLE and institute appropriate medical intervention.

5.7 Bone Fracture

Epidemiological studies on bone fracture risk following exposure to SSRIs have reported an association between SSRI treatment and fractures. It is unknown to what extent fracture risk is directly attributable to SSRI treatment. If a BRISDELLE-treated patient presents with unexplained bone pain, point tenderness, swelling, or bruising, consider the possibility of a fragility fracture.

5.8 Screening Patients for Bipolar Disorder and Monitoring for Mania/Hypomania

BRISDELLE is only indicated for the treatment of moderate to severe VMS and is not approved for use in treating either depression or bipolar depression. However, prior to initiating treatment with BRISDELLE, all patients should be adequately screened to determine if they are at risk for bipolar disorder; such screening should include a detailed psychiatric history, including a family history of suicide, bipolar disorder, and depression. It is generally believed (though not established in controlled trials) that use of an antidepressant alone may increase the likelihood of precipitation of a mixed/manic episode in patients at risk for bipolar disorder.

5.9 Seizures

In clinical studies of another paroxetine product, seizures occurred in 0.1% of paroxetine-treated patients.

Use BRISDELLE cautiously in patients with a history of seizures or with conditions that potentially lower the seizure threshold. Discontinue BRISDELLE in any patient who develops seizures.

5.10 Sexual Dysfunction

Use of SSRIs, including BRISDELLE, may cause symptoms of sexual dysfunction. In female patients, SSRI use may result in decreased libido and delayed or absent orgasm.

It is important for prescribers to inquire about sexual function prior to initiation of BRISDELLE and to inquire specifically about changes in sexual function during treatment because sexual function may not be spontaneously reported. When evaluating changes in sexual function, obtaining a detailed history (including timing of symptom onset) is important because sexual symptoms may have other causes. Discuss potential management strategies to support patients in making informed decisions about treatment.

6 ADVERSE REACTIONS

The following serious adverse reactions are discussed elsewhere in labeling:

- Suicidality [see Warnings and Precautions (5.1)]
- Serotonin syndrome [see Warnings and Precautions (5.2)]
- Abnormal bleeding [see Warnings and Precautions (5.4)]
- Angle-Closure Glaucoma [see Warnings and Precautions (5.5)]
- Hyponatremia [see Warnings and Precautions (5.6)]
- Bone Fracture [see Warnings and Precautions (5.7)]
- Mania/Hypomania [see Warnings and Precautions (5.8)]
- Seizure [see Warnings and Precautions (5.9)]

6.1 Clinical Trials Experience

Because clinical trials are conducted under widely varying conditions, adverse reaction rates observed in the clinical trials of a drug cannot directly be compared to rates in the clinical trials of another drug and may not reflect the rates observed in practice.

The data described below reflect exposure to BRISDELLE in the following randomized, placebo-controlled trials for the treatment of moderate to severe VMS associated with menopause [see Clinical Studies (14)]: (1) one 8-week Phase 2 trial, (2) one 12-week Phase 3 trial and (3) one 24-week Phase 3 trial. In these trials, a total of 635 postmenopausal females received BRISDELLE 7.5 mg administered orally once daily and 641 postmenopausal females received placebo. In these trials, 68% were White, 30% were Black or African American (30%), and 2% were other races, with a mean age of 55 years (range 40 to 73 years). Postmenopausal females with a history of suicidal ideation or suicidal behavior were excluded from these trials.

Serious Adverse Reactions:

In the pooled Phase 2 and Phase 3 trials, three BRISDELLE-treated patients reported a serious adverse reaction of suicidal ideation and one BRISDELLE-treated patient reported a serious adverse reaction of suicide attempt. There were no serious adverse reactions of suicidal ideation or suicide attempt reported among the placebo-treated patients.

Adverse Reactions Leading to Study Discontinuation:

A total of 4.7% of females taking BRISDELLE discontinued from the clinical trials due to an adverse reaction, compared to 3.7% of females on placebo; the most frequent adverse reactions leading to discontinuation among paroxetine-treated females were: abdominal pain (0.3%), attention disturbances (0.3%), headache (0.3%), and suicidal ideation (0.3%).

Common Adverse Reactions:

Overall, based on investigators’ determinations about what events were likely to be drug-related, about 20% of postmenopausal females treated with BRISDELLE reported at least 1 adverse reaction in the three controlled trials. The most common adverse reactions (≥ 2% and at a higher incidence in BRISDELLE-treated females compared to placebo-treated females) reported in these trials were headache, fatigue/malaise/lethargy, and nausea/vomiting. Of these commonly reported adverse reactions, nausea occurred primarily within the first 4 weeks of BRISDELLE treatment and fatigue occurred primarily within the first week of BRISDELLE treatment, and decreased in frequency with continued therapy.

The adverse reactions that occurred in ≥ 2% of BRISDELLE-treated patients and at a higher incidence in BRISDELLE-treated females compared to placebo-treated females are shown in Table 1 for the pooled Phase 2 and Phase 3 trials.

Table 1: Incidence of Common Adverse Reactions in the Phase 2 and Phase 3 Trials of Postmenopausal Females with Moderate to Severe VMS^1

 | Incidence n (%)
 | BRISDELLE (n = 635) | BRISDELLE (n = 641)
Headache | 40 (6.3) | 31 (4.8)
Fatigue, malaise, lethargy | 31 (4.9) | 18 (2.8)
Nausea, vomiting | 27 (4.3) | 15 (2.3)

^1 ≥ 2% BRISDELLE-treated patients and at a higher incidence in BRISDELLE-treated females compared to placebo-treated females.

Adverse Reactions After Discontinuing BRISDELLE

Certain symptoms were seen more frequently in postmenopausal females at the time of discontinuation of BRISDELLE compared to discontinuation of placebo and have also been reported upon discontinuation of other paroxetine products, particularly after abrupt discontinuation. Adverse reactions reported after discontinuation of BRISDELLE included increased dreaming/nightmares, muscle cramps/spasms/twitching, headache, nervousness/anxiety, fatigue/tiredness, restless feeling in legs, and trouble sleeping/insomnia. While these adverse reactions were generally self-limiting, there have been reports of serious discontinuation symptoms with other paroxetine products.

6.2 Postmarketing Experience

The following adverse reactions have been identified during post-approval use of this and other paroxetine products. Because some of these reactions are reported voluntarily from a population of uncertain size, it is not always possible to reliably estimate their frequency or establish a causal relationship to drug exposure.

Blood and Lymphatic System Disorders: Idiopathic thrombocytopenic purpura, Events related to impaired hematopoiesis (including aplastic anemia, pancytopenia, bone marrow aplasia, agranulocytosis).

Cardiac Disorders: Atrial fibrillation, Pulmonary edema, Ventricular fibrillation, Ventricular tachycardia (including torsades de pointes).

Gastrointestinal Disorders: Pancreatitis, Pancreatitis hemorrhagic, Vomiting.

General Disorders and Administration Site Conditions: Death, Drug withdrawal syndrome, Malaise.

Hepatobiliary Disorders: Drug-induced liver injury, Hepatic failure, Jaundice.

Immune System Disorders: Anaphylaxis, Angioedema, Toxic epidermal necrolysis.

Investigations: Elevated liver tests (the most severe cases were deaths due to liver necrosis, and grossly elevated transaminases associated with severe liver dysfunction).

Metabolism and Nutrition Disorders: Diabetes mellitus inadequate control, Type 2 diabetes mellitus.

Nervous System Disorders: Neuroleptic malignant syndrome, Paresthesia, Somnolence, Tremor, Anosmia, Hyposmia

Psychiatric Disorders: Aggression, Agitation, Anxiety, Confusional state, Depression, Disorientation, Homicidal ideation, Insomnia, Restlessness.

Respiratory, Thoracic and Mediastinal Disorders: Pulmonary hypertension.

Skin and Subcutaneous Tissue Disorders: Hyperhidrosis, Stevens-Johnson syndrome, Drug reaction with eosinophilia and systemic symptoms (DRESS).

7 DRUG INTERACTIONS

7.1 Potential for BRISDELLE to Affect Other Drugs

Paroxetine is a strong CYP2D6 inhibitor. Clinical drug interaction studies have been performed with substrates of CYP2D6 and show that paroxetine can inhibit the metabolism of drugs metabolized by CYP2D6 [see Clinical Pharmacology (12.3)]. Table 2 contains examples of drugs with a metabolism that may be affected by concomitant use with BRISDELLE.

Table 2 Effects of Paroxetine on Other Drugs

Concomitant Drug Name | Effect of Paroxetine on Other Drugs | Clinical Recommendations
Thioridazine | Increased plasma concentrations of thioridazine Potential QTc prolongation | Concomitant use of thioridazine and BRISDELLE is contraindicated.
Pimozide | Increased plasma concentrations of pimozide. Potential QTc prolongation | Concomitant use of pimozide and BRISDELLE is contraindicated.
Tamoxifen | Reduced plasma concentrations of active tamoxifen metabolite | Consider avoiding concomitant use of tamoxifen and BRISDELLE.
Tricyclic Antidepressants (TCA) (e.g., Desipramine) | Increased plasma concentrations and elimination half-life | Plasma TCA concentrations may need to be monitored and the TCA dosage may need to be reduced if a TCA is used concomitantly with BRISDELLE. Monitor tolerability.
Risperidone | Increased plasma concentrations of risperidone | A lower risperidone dosage may be necessary (see the risperidone Prescribing Information for). Monitor tolerability.
Atomoxetine | Increased exposure of atomoxetine | A lower atomoxetine dosage of may be necessary (see atomoxetine Prescribing Information for). Monitor tolerability.
Drugs Highly Bound to Plasma Protein (e.g., Warfarin) | Increased free plasma concentrations | The warfarin dosage may need to be reduced. Monitor tolerability and the International Normalized Ratio.
Digoxin | Decreased plasma concentrations of digoxin | The digoxin dosage of may need to be increased. Monitor digoxin concentrations and clinical effect.
Theophylline | Increased plasma concentrations of theophylline | The theophylline dosage of may need to be decreased. Monitor theophylline concentrations and tolerability.

Use caution with concomitant use of BRISDELLE with other drugs that are metabolized by CYP2D6, including nortriptyline, amitriptyline, imipramine, desipramine, fluoxetine, phenothiazines, risperidone, and Type 1C antiarrhythmics (e.g., propafenone, flecainide, and encainide).

7.2 Potential for Other Drugs to Affect BRISDELLE

The metabolism and pharmacokinetics of paroxetine may be affected by the induction and inhibition of drug metabolizing enzymes such as CYP2D6. Table 3 contains a list of drugs that may affect the pharmacokinetics of BRISDELLE when administered concomitantly [see Clinical Pharmacology (12.3)].

Table 3 Effects of Other Drugs on Paroxetine

Concomitant Drug Name | Effect of Concomitant Drug on Paroxetine | Clinical Recommendations
Phenobarbital | Decreased paroxetine exposure
Phenytoin | Decreased paroxetine exposure
Fosamprenavir/Ritonavir | Decreased plasma concentration of paroxetine | Monitor clinical effect of BRISDELLE. No BRISDELLE dosage adjustment is needed.
Cimetidine | Increased plasma concentration of paroxetine

Use caution if BRISDELLE is used concomitantly with other drugs that inhibit CYP2D6 (e.g., quinidine).

7.3 Other Potentially Significant Drug Interactions

Monoamine Oxidase Inhibitors

Serious adverse reactions such as serotonin syndrome have been reported in patients treated with a SSRI and a concomitant monoamine oxidase inhibitor (MAOI), in patients started on an SSRI who recently received an MAOI and in patients started on an MAOI who recently received an SSRI. Therefore, concomitant use of MAOIs with BRISDELLE or use of BRISDELLE and an MAOI within 14 days of each other is contraindicated [see Dosage and Administration (2.2), Contraindications (4.1) and Warnings and Precautions (5.2)].

Serotonergic Drugs

If concomitant use of BRISDELLE with other serotonergic drugs (e.g., other SNRIs, SSRIs, triptans, tricyclic antidepressants, opioids, lithium, tryptophan, buspirone, amphetamines, and St. John’s Wort) is clinically warranted, consider the increased risk of serotonin syndrome and carefully observe the patient, particularly during treatment initiation [see Warnings and Precautions (5.2)].

An interaction between paroxetine and tryptophan may occur when they are co-administered. Adverse reactions, consisting primarily of headache, nausea, sweating, and dizziness, have been reported when tryptophan was administered to patients taking paroxetine. Consequently, concomitant use of BRISDELLE with tryptophan is not recommended.

Drugs that Interfere with Hemostasis (e.g., NSAIDs, Aspirin, and Warfarin)

Altered anticoagulant effects, including increased bleeding, have been reported when SSRIs are concomitantly administered with NSAIDs, aspirin, warfarin. or other drugs that affect coagulation. There may be a pharmacodynamic interaction between paroxetine and warfarin that causes an increased bleeding diathesis despite unaltered prothrombin time. Carefully monitor patients receiving warfarin therapy when BRISDELLE is initiated or discontinued [see Warnings and Precautions (5.4)].

8 USE IN SPECIFIC POPULATIONS

8.1 Pregnancy

Risk Summary

BRISDELLE is contraindicated in pregnant females and not indicated for use in pre-menopausal females. Based on epidemiologic and animal studies, paroxetine can cause fetal harm. Based on data from published observational studies, exposure to SSRIs, particularly in the month before delivery, has been associated with a less than 2-fold increase in the risk of postpartum hemorrhage [see Warnings and Precautions (5.4)].

Paroxetine is associated with a less than 2-fold increase in cardiovascular malformations when administered to a pregnant female during the first trimester. While individual epidemiological studies on the association between paroxetine use and cardiovascular malformations have reported inconsistent findings, some meta-analyses of epidemiological studies have identified an increased risk of cardiovascular malformations (see Data). There are risks of persistent pulmonary hypertension of the newborn (PPHN) (see Data) and/or poor neonatal adaptation with exposure to selective serotonin reuptake inhibitors (SSRIs), including BRISDELLE, during pregnancy.

No evidence of treatment related malformations was observed in animal reproduction studies, when paroxetine was administered during the period of organogenesis at doses up to 50 mg/kg/day in rats and 6 mg/kg/day in rabbits. These doses are approximately 64 times (rat) and less than 16 times (rabbit) the maximum recommended human dose (MRHD) of BRISDELLE (7.5 mg) on an mg/m^2 basis. When paroxetine was administered to female rats during the last trimester of gestation and continued through lactation, there was an increase in the number of pup deaths during the first four days of lactation. This effect occurred at a dose of 1 mg/kg/day which is 1.3 times the MRHD on an mg/m^2 basis (see Data).

Data

Human Data: Published epidemiological studies on the association between first trimester paroxetine use and cardiovascular malformations have reported inconsistent results; however, meta-analyses of population-based cohort studies published between 1996-2017 indicate a less than 2-fold increased risk for overall cardiovascular malformations. Specific cardiac malformations identified in two meta-analyses include approximately 2 to 2.5-fold increased risk for right ventricular outflow tract defects. One meta-analysis also identified an increased risk (less than 2-fold) for bulbus cordis anomalies and anomalies of cardiac septal closure, and an increased risk for atrial septal defects (pooled OR 2.38, 95% CI 1.14-4.97). Important limitations of the studies included in these meta-analyses include potential confounding by indication, depression severity, and potential exposure misclassification.

Exposure to SSRIs, particularly later in pregnancy, may have an increased risk for PPHN. PPHN occurs in 1-2 per 1000 live births in the general population and is associated with substantial neonatal morbidity and mortality.

Animal Data: Reproduction studies were performed at doses up to 50 mg/kg/day in rats and 6 mg/kg/day in rabbits administered during organogenesis. These doses are approximately 64 times (rat) and less than 16 times (rabbit) MRHD of BRISDELLE (7.5 mg) on an mg/m^2 basis. These studies have revealed no evidence of malformations. However, in rats, there was an increase in pup deaths during the first 4 days of lactation when dosing occurred during the last trimester of gestation and continued throughout lactation. This effect occurred at a dose of 1 mg/kg/day which is 1.3 times the MRHD on an mg/m^2 basis. The no effect dose for rat pup mortality was not determined. The cause of these deaths is not known.

8.4 Pediatric Use

Safety and effectiveness of BRISDELLE in pediatric patients have not been established; BRISDELLE is not indicated in the pediatric population.

8.5 Geriatric Use

Clinical trials of BRISDELLE did not include sufficient numbers of patients aged 65 and over to determine whether they respond differently from younger adult patients. Patients 65 years of age and older may have elevated paroxetine plasma concentrations compared to younger adult patients. However, the recommended BRISDELLE dosage in patients 65 years of age and older is that same as that as younger patients [see Clinical Pharmacology (12.3)].

SSRIs have been associated with cases of clinically significant hyponatremia in geriatric patients, who may be at greater risk for this adverse reaction [see Warnings and Precautions (5.6)].

8.6 Renal Impairment

The recommended BRISDELLE dosage in patients with renal impairment is the same as those with normal renal function [see Clinical Pharmacology (12.3)].

8.7 Hepatic Impairment

The recommended BRISDELLE dosage in patients with hepatic impairment is the same as those with normal hepatic function [see Clinical Pharmacology (12.3)].

10 OVERDOSAGE

The following have been reported with paroxetine tablets overdose:

- Seizures, which may be delayed, and altered mental status including coma.
- Cardiovascular toxicity, which may be delayed, including QRS and QTc interval prolongation. Hypertension most commonly seen, but rarely can see hypotension alone or with co-ingestants including alcohol.
- Serotonin syndrome (patients with a multiple drug overdosage with other pro-serotonergic drugs may have a higher risk).

Consider contacting the Poison Help Line (1-800-221-2222) or a medical toxicologist for overdose management recommendations.

11 DESCRIPTION

BRISDELLE (paroxetine) is an orally administered selective serotonin reuptake inhibitor (SSRI) for the treatment of moderate to severe VMS associated with menopause. It is identified chemically as (-)-trans-4R- (4’-fluorophenyl) - 3S - [(3’, 4’-methylenedioxyphenoxy) methyl] piperidine mesylate and has the empirical formula of C19H20FNO3•CH3SO3H. The molecular weight is 425.5 (329.4 as free base). The structural formula is:

The mesylate salt of paroxetine is an odorless, off-white powder, having a melting point range of 147° to 150°C and a solubility of more than 1 g/mL in water.

Each pink capsule contains 9.69 mg of paroxetine mesylate equivalent to 7.5 mg paroxetine base.

Inactive ingredients consist of: dibasic calcium phosphate, sodium starch glycolate, magnesium stearate, gelatin, titanium dioxide, FD&C Yellow #6, FD&C Red #3, FD&C Red #40, shellac, and black iron oxide.

12 CLINICAL PHARMACOLOGY

12.1 Mechanism of Action

Nonclinical studies have shown that paroxetine is an SSRI; BRISDELLE is not an estrogen. The mechanism of action of BRISDELLE for the treatment of moderate to severe VMS associated with menopause is unknown.

Studies at clinically relevant BRISDELLE doses in humans have demonstrated that paroxetine blocks the uptake of serotonin into human platelets. Paroxetine is a neuronal serotonin reuptake inhibitor with weak effects on norepinephrine and dopamine neuronal reuptake in vitro. Paroxetine also has low affinity for muscarinic alpha1-, alpha2-, beta-adrenergic, dopamine (D2)-, 5-HT1-, 5-HT2-, and histamine (H1)-receptors.

12.2 Pharmacodynamics

The exposure-response relationship and time course of pharmacodynamic response for the safety and effectiveness of paroxetine for the treatment of moderate to severe VMS associated with menopause have not been fully characterized.

12.3 Pharmacokinetics

Absorption

Paroxetine is completely absorbed after oral dosing.

In a study in which healthy postmenopausal females (n=24) received BRISDELLE 7.5 mg once daily for 14 days, steady-state paroxetine concentrations were achieved by approximately 12 days of dosing for most subjects, although it may take substantially longer in an occasional patient. Peak concentrations were reached at a median of 6 hours (3 to 8 hours range). Steady-state mean values of Cmax, Cmin, and AUC0-last were 13.10 ng/mL (CV 91%), 7.17 ng/mL (CV 99%), and 237 hr*ng/mL (CV 94%), respectively.

Steady-state AUC0-24 values were about 3 times those of AUC0-inf following a single BRISDELLE dose, indicating non-linear pharmacokinetics. Steady-state Cmax values were approximately 5 times greater than those attained after a single BRISDELLE dose and steady-state exposure based on AUC0-24 was about 10 times greater than AUC0-24 after a single dose.

The nonlinear kinetics and excess accumulation are due to the fact that CYP2D6, an enzyme that is in part responsible for paroxetine metabolism, is readily saturable.

Effect of Food: The effects of food on the bioavailability of paroxetine were studied after administration of another paroxetine product with a dosage higher than BRISDELLE. AUC was slightly increased (6%) when paroxetine was administered with food and the Cmax was 29% greater, while the time to reach peak plasma concentration decreased from 6.4 hours post-dosing to 4.9 hours. These changes are not clinically significant [see Dosage and Administration (2.1)].

Distribution

Paroxetine distributes throughout the body, including the central nervous system, with only 1% remaining in the plasma.

Approximately 95% and 93% of paroxetine is bound to plasma protein at 100 ng/mL and 400 ng/mL, respectively. Paroxetine does not alter the in vitro protein binding of phenytoin or warfarin.

Elimination

Metabolism: Paroxetine is extensively metabolized after oral administration. The principal metabolites are polar and conjugated products of oxidation and methylation, which are readily cleared. Conjugates with glucuronic acid and sulfate predominate, and major metabolites have been isolated and identified. Data indicate that the metabolites have no more than 1/50 the potency of the parent compound at inhibiting serotonin uptake. The metabolism of paroxetine is accomplished in part by cytochrome CYP2D6. The role of this enzyme in paroxetine metabolism also suggests potential drug interactions [see Drug Interactions (7)]. At steady state, when the CYP2D6 pathway is essentially saturated, paroxetine clearance is governed by alternative P450 isozymes, which, unlike CYP2D6, show no evidence of saturation.

Excretion: Approximately 64% of a 30 mg oral solution of another paroxetine product (four times the recommended BRISDELLE dosage) was excreted in the urine with 2% as the parent compound and 62% as metabolites over a 10-day post-dosing period. About 36% of the dose was excreted in the feces (probably via the bile), mostly as metabolites and less than 1% as the parent compound over the 10-day post-dosing period.

Specific Populations

Patients with Renal and Hepatic Impairment: Increased plasma concentrations of paroxetine occur in subjects with renal and hepatic impairment. The mean plasma concentration in patients with creatinine clearance below 30 mL/min was approximately 4 times greater than seen in normal volunteers. Patients with creatinine clearance of 30 to 60 mL/min and patients with hepatic impairment had about a 2-fold increase in plasma concentrations (AUC, Cmax) [see Use in Specific Populations (8.6, 8.7)].

Geriatric Patients: In a multiple-dose study in geriatric patients with another paroxetine product at doses of 20, 30, and 40 mg (1.7, 4, and 5.3, times the maximum recommended BRISDELLE dosage, respectively), Cmin concentrations were about 70% to 80% greater than the respective Cmin concentrations in younger adult subjects [see Use in Specific Populations (8.5)].

Drug Interaction Studies

Potential Effect of BRISDELLE on Other Drugs

- Drugs Metabolized by CYP3A4: An in vivo drug interaction study involving the concomitant use of paroxetine and terfenadine, a substrate for cytochrome CYP3A4, under steady-state conditions revealed no effect of paroxetine on terfenadine pharmacokinetics. In vitro studies have shown ketoconazole, a potent CYP3A4 inhibitor, to be at least 100 times more potent than paroxetine as an inhibitor of the metabolism of several substrates for CYP3A4, including astemizole, triazolam, and cyclosporine. Based on the assumption that the relationship between paroxetine’s in vitro Ki and its lack of effect on terfenadine’s in vivo clearance predicts its effect on other CYP3A4 substrates, paroxetine’s extent of CYP3A4 inhibition is not likely to be of clinical significance.
- Drugs Metabolized by CYP2D6: Many drugs are metabolized by the cytochrome P450 isozyme CYP2D6. Like other agents that are metabolized by CYP2D6, paroxetine may significantly inhibit the activity of this isozyme. In most patients (> 90%), this CYP2D6 isozyme is saturated early during paroxetine dosing. Specific studies investigating the effect of paroxetine on drugs metabolized by CYP2D6 are listed below:
  - Pimozide: In a controlled study of healthy volunteers, after another paroxetine product was titrated to 60 mg daily (8 times the maximum recommended BRISDELLE dosage), concomitant use of paroxetine with a single 2 mg dose of pimozide was associated with mean increases in pimozide AUC of 151% and Cmax of 62%, compared to pimozide administered alone [see Drug Interactions (7.1)].
  - Desipramine: In one study, daily dosing of another paroxetine product (20 mg once daily) (2.7 times the recommended BRISDELLE dosage) under steady-state conditions with a concomitant single dose of desipramine (100 mg) increased desipramine Cmax, AUC, and T½ by an average of approximately 2-, 5-, and 3-fold, respectively [see Drug Interactions (7.1)].
  - Risperidone: Daily dosing of another paroxetine product at 20 mg in patients stabilized on risperidone (4 to 8 mg/day), a CYP2D6 substrate, increased mean plasma risperidone concentrations approximately 4-fold, decreased 9-hydroxyrisperidone concentrations approximately 10%, and increased concentrations of the active moiety (the sum of risperidone plus 9-hydroxyrisperidone) approximately 1.4-fold [see Drug Interactions (7.1)].
  - Atomoxetine: The effect of paroxetine on the pharmacokinetics of atomoxetine has been evaluated when both drugs were at steady state. In healthy volunteers who were extensive metabolizers of CYP2D6, 20 mg daily of another paroxetine product was given in combination with 20 mg atomoxetine every 12 hours resulting in increases in steady-state atomoxetine AUC values that were 6- to 8-fold greater and in atomoxetine Cmax values that were 3- to 4-fold greater than when atomoxetine was given alone [see Drug Interactions (7.1)].
  - Digoxin: Mean digoxin AUC at steady state decreased by 15% in the presence of paroxetine [see Drug Interactions (7.1)].
  - Beta Blockers: In a study in which propranolol (80 mg twice daily) was dosed orally for 18 days, the steady-state plasma concentrations of propranolol were unaltered during concomitant use with another paroxetine product (30 mg once daily) (4 times the recommended BRISDELLE dosage) for the final 10 days. The effects of propranolol on paroxetine have not been evaluated.

Potential Effect of Other Drugs on BRISDELLE

Concomitant use of paroxetine with other drugs that alter CYP enzymes activities including CYP2D6 may affect the plasma concentrations of paroxetine. Specific studies investigating the effect of other drugs on paroxetine are listed below:

- Cimetidine: Cimetidine inhibits many cytochrome P450 enzymes. In a study in which another paroxetine product was dosed orally at 30 mg once daily (4 times the recommended BRISDELLE dosage) for 4 weeks, steady-state plasma concentrations of paroxetine were increased by approximately 50% during concomitant use with oral cimetidine (300 mg three times daily) for the final week [see Drug Interactions (7.2)].
- Phenobarbital: Phenobarbital induces many cytochrome P450 enzymes. When a single oral 30 mg dose of another paroxetine product (4 times the recommended BRISDELLE dosage) was administered at phenobarbital steady state (100 mg once daily for 14 days), paroxetine AUC and T½ were reduced (by an average of 25% and 38%, respectively) compared to paroxetine administered alone. The effect of paroxetine on phenobarbital pharmacokinetics was not studied. Because paroxetine exhibits nonlinear pharmacokinetics, the results of this study may not address the case where the two drugs are both being chronically dosed [see Drug Interactions (7.2)].
- Phenytoin: When a single oral 30 mg dose of another paroxetine product (4 times the recommended BRISDELLE dosage) was administered at phenytoin steady state (300 mg once daily for 14 days), paroxetine AUC and T½ were reduced (by an average of 50% and 35%, respectively) compared to paroxetine administered alone. In a separate study, when a single oral 300 mg dose of phenytoin was administered with another paroxetine product (30 mg once daily for 14 days) at paroxetine steady state, phenytoin AUC was slightly reduced (12% on average) compared to phenytoin administered alone. Because both drugs exhibit nonlinear pharmacokinetics, the above studies may not address the case where the two drugs are both being chronically dosed [see Drug Interactions (7.2)].
- Digoxin: A clinical drug interaction study showed that concurrent use of digoxin did not affect paroxetine exposure.
- Diazepam: A clinical drug interaction study showed that concurrent use of diazepam did not affect paroxetine exposure.

13 NONCLINICAL TOXICOLOGY

13.1 Carcinogenesis, Mutagenesis, Impairment of Fertility

Carcinogenesis

Two-year carcinogenicity studies were conducted in rodents given paroxetine in the diet at 1, 5, and 25 mg/kg/day (mice) and 1, 5, and 20 mg/kg/day (rats). The doses used in these carcinogenicity studies were approximately 16 (mouse) and 26 (rat) times the MHRD for BRISDELLE for the treatment of moderate to severe VMS associated with menopause. There was a significantly greater number of male rats in the high-dose group with reticulum cell sarcomas (1/100, 0/50, 0/50, and 4/50 for control, low-, middle-, and high-dose groups, respectively) and a significantly increased linear trend across groups for the occurrence of lymphoreticular tumors in male rats. Female rats were not affected. Although there was a dose-related increase in the number of tumors in mice, there was no paroxetine -related increase in the number of mice with tumors. The relevance of these findings to humans is unknown.

Mutagenesis

Paroxetine produced no genotoxic effect in a battery of 5 in vitro and 2 in vivo assays that included the following: bacterial mutation assay, mouse lymphoma mutation assay, unscheduled DNA synthesis assay, and tests for cytogenetic aberrations in vivo in mouse bone marrow and in vitro in human lymphocytes and in a dominant lethal test in rats.

14 CLINICAL STUDIES

The effectiveness of BRISDELLE as a treatment for moderate to severe vasomotor symptoms (VMS) associated with menopause was established in two Phase 3 randomized, double-blind, placebo-controlled clinical trials in 1,174 postmenopausal females. In these trials, patients must have had a minimum of 7-8 moderate to severe VMS per day at baseline (≥ 50 per week) for 30 days prior to receiving study drug. Patients were randomized to BRISDELLE 7.5 mg orally once daily or daily placebo:

- Trial 1 was a 12-week trial with a total of 606 postmenopausal females (average age 55 years; 65% White, 33% Black or African American, and 2% other races; 10.6% were Hispanic/Latina and 89.4% were not Hispanic/Latina; 18% surgically menopausal and 82% naturally menopausal).
- Trial 2 was a 24-week trial with a total of 568 postmenopausal females (average age 54 years; 76% White, 22% Black or African American, and 2% other races; 6.5% were Hispanic/Latina and 93.5% were not Hispanic/Latina; 20% surgically menopausal and 81% naturally menopausal).

The co-primary efficacy endpoints for both trials were the reduction from baseline in VMS frequency and VMS severity at Weeks 4 and 12.

- Data from Trial 1 showed a statistically significant reduction from baseline in the frequency of moderate to severe VMS at Week 4 and Week 12 and a statistically significant reduction in the severity of moderate to severe VMS at Week 4 in the BRISDELLE group compared to the placebo group (Table 4).
- Data from Trial 2 showed a statistically significant reduction from baseline in the frequency and severity of moderate to severe VMS at Week 4 and Week 12 in the BRISDELLE group compared to placebo group (Table 5).

Table 4: Trial 1: Changes in the Daily Frequency and Daily Severity of VMS at Weeks 4 and 12 in Postmenopausal Females with Moderate to Severe VMS (MITT Population)

 | Frequency |  | Severity
 | BRISDELLE | Placebo | BRISDELLE | Placebo
Baseline
n | 301 | 305 | 301 | 305
Median | 10.4 | 10.4 | 2.5 | 2.5
Change from baseline at Week 4
n | 289 | 293 | 281 | 289
Median | -4.3 | -3.1 | -0.05 | 0.00
Treatment Difference* | -1.2 |  | -0.05
P-value# | <0.01 |  | <0.01
Change from baseline at Week 12
n | 264 | 274 | 236 | 253
Median | -5.9 | -5.0 | -0.06 | -0.02
Treatment Difference* | -0.9 |  | -0.04
P-value# | <0.01 |  | 0.17

MITT population: all consented and randomized patients with valid baseline daily hot flash diary data who had taken at least 1 dose of study drug and had at least 1 day of on-treatment daily hot flash diary data.
* Treatment Difference: the difference between the median changes from baseline.
# P-value was obtained from rank-ANCOVA model.

Table 5: Trial 2: Changes in the Daily Frequency and Daily Severity of VMS at Weeks 4 and 12 in Postmenopausal Females with Moderate to Severe VMS (MITT Population)

 | Frequency |  | Severity
 | BRISDELLE | Placebo | BRISDELLE | Placebo
Baseline
n | 284 | 284 | 284 | 284
Median | 9.9 | 9.6 | 2.5 | 2.5
Change from baseline at Week 4
n | 276 | 274 | 268 | 271
Median | -3.8 | -2.5 | -0.04 | -0.01
Treatment Difference* | -1.3 |  | -0.03
P-value# | <0.01 |  | 0.04
Change from baseline at Week 12
n | 257 | 244 | 245 | 236
Median | -5.6 | -3.9 | -0.05 | 0.00
Treatment Difference* | -1.7 |  | -0.05
P-value# | <0.01 |  | <0.01

MITT population: all consented and randomized patients with valid baseline daily hot flash diary data who had taken at least 1 dose of study drug and had at least 1 day of on-treatment daily hot flash diary data.
* Treatment Difference: the difference between the median changes from baseline.
# P-value is obtained from rank-ANCOVA model.

Persistence of benefit at 24 weeks in Trial 2 was evaluated with a responder analysis where responders were defined as those patients who achieved ≥ 50% reduction from baseline in the frequency of moderate to severe VMS at Week 24. The proportion of patients who achieved a ≥ 50% reduction in the frequency of moderate to severe VMS from baseline to Week 24 was 48% in the BRISDELLE group and 36% in the placebo group at Week 24.

16 HOW SUPPLIED/STORAGE AND HANDLING

BRISDELLE (paroxetine) capsules is available as 7.5 mg pink capsules printed with black edible ink with “BRISDELLE” and “7.5 mg”.

NDC 83107-027-30 blister packs of 30

Store at 20°-25°C (68°-77°F); excursions permitted to 15°-30°C (59°-86°F). Protect from light and humidity.

17 PATIENT COUNSELING INFORMATION

Advise the patient to read the FDA-approved patient labeling (Medication Guide).

Instruct patients to read the Medication Guide before starting therapy with BRISDELLE and to reread it each time the prescription is renewed.

Suicidal Thoughts and Behaviors

Advise patients, their families, and their caregivers to look for the emergence of suicidal thoughts and behaviors, especially early during treatment and to alert the health care provider if such changes occur [see Boxed Warning and Warnings and Precautions (5.1)].

Serotonin Syndrome

Caution patients about the risk of serotonin syndrome, particularly with the concomitant use of BRISDELLE with triptans, tricyclic antidepressants, opioids, linezolid, tramadol, amphetamines, St. John’s Wort, lithium, tryptophan supplements, other serotonergic agents, or antipsychotic drugs. Instruct patients to contact their health care provider, or report to the emergency room, should they experience signs or symptoms of serotonin syndrome [see Warnings and Precautions (5.2) and Drug Interactions (7.3)].

Potential Impact on Tamoxifen Efficacy

Caution patients that efficacy of tamoxifen may be reduced when administered concomitantly and counsel them about the likely benefit of paroxetine for treating VMS vs. the risk of possible decreased tamoxifen effectiveness [see Warnings and Precautions (5.3)].

Increased Risk of Bleeding

Caution patients about the concomitant use of BRISDELLE and NSAIDs, aspirin, warfarin, and other anticoagulants because combined use of drugs that interfere with serotonin reuptake has been associated with an increased risk of bleeding [see Warnings and Precautions (5.4)].

Angle-Closure Claucoma

Advise patients that taking BRISDELLE can cause mild pupillary dilation, which in susceptible individuals, can lead to an episode of angle-closure glaucoma -existing [See Warnings and Precautions (5.5)].

Hyponatremia

Caution patients about the risk of hyponatremia, particularly elderly patients and those who are taking diuretics or are volume-depleted [see Warnings and Precautions (5.6)].

Bone Fracture

Inform patients that there is the possibility for an increased risk of fracture [see Warnings and Precautions (5.7)].

Screening Patients for Bipolar Disorder and Monitoring for Mania/Hypomania

Advise patients, their families, and their caregivers to observe for signs of activation of mania/hypomania [see Warnings and Precautions (5.8)].

Pregnancy

Advise patients to notify their physician if they become pregnant during therapy [see Contraindications (4.5) and Use in Specific Populations (8.1)].

Drug Interactions

Advise patients to inform their healthcare provider if they are taking, or plan to take, any prescription or over-the-counter drugs, including herbal supplements, because there is a potential for interaction with paroxetine [see Drug Interactions (7)].

Sexual Dysfunction

Advise patients that use of BRISDELLE may cause symptoms of sexual dysfunction in female patients. Inform patients that they should discuss any changes in sexual function and potential management strategies with their healthcare provider [see Warnings and Precautions (5.10)].

Allergic Reactions

Advise patients to seek medical attention if they develop an allergic reaction such as rash, hives, swelling, or difficulty breathing [see Adverse Reactions (6.2)].

BRISDELLE is a registered trademark of Legacy Pharma Inc.

©2025 Legacy Pharma Inc. All rights reserved.

Manufactured for:
Legacy Pharma Inc.
George Town, Grand Cayman
KY1-9012

MEDICATION GUIDE

BRISDELLE® (bris-del)

(paroxetine)

capsules

Read this Medication Guide that comes with BRISDELLE before you start taking it and each time you get a refill. There may be new information. This information does not take the place of talking to your healthcare provider about your medical condition or treatment. Talk with your healthcare provider if there is something you do not understand or want to learn more about.

What is the most important information I should know about BRISDELLE?

BRISDELLE may cause serious side effects, including:

- Increased risk of suicidal thoughts or actions. BRISDELLE and related antidepressant medicines may increase suicidal thoughts or actions within the first few months of treatment.
  - Depression or other serious mental illnesses are the most important causes of suicidal thoughts or actions.
  - Watch for these changes and call your healthcare provider right away if you notice:
    - New or sudden changes in mood, behavior, actions, thoughts, or feelings, especially if severe.
    - Pay close attention to any changes when BRISDELLE is started.
  - Keep all follow-up visits with your healthcare provider and call between visits if you are worried about symptoms.

Call your healthcare provider right away or go to the nearest emergency room if you have any of the following symptoms, especially if they are new, worse, or worry you:

- attempts to commit suicide
- acting on dangerous impulses
- acting aggressive or violent
- thoughts about suicide or dying
- new or worse depression
- new or worse anxiety or panic attacks
- feeling agitated, restless, angry or irritable
- trouble sleeping
- an increase in activity or talking more than what is normal for you
- other unusual changes in behavior or mood

What is BRISDELLE?

- BRISDELLE is a prescription medicine used to treat moderate to severe hot flashes associated with menopause.
- BRISDELLE is not any for psychiatric problems such as depression, obsessive compulsive disorder, panic disorder, generalized anxiety disorder, social anxiety disorder, and post-traumatic stress disorder.
- BRISDELLE is not for use in children.

Who should not take BRISDELLE?

Do not take BRISDELLE if you:

- take a Monoamine Oxidase Inhibitor (MAOI). Ask your healthcare provider or pharmacist if you are not sure if you take an MAOI, including the antibiotic linezolid or the intravenous methylene blue.
  - Do not take an MAOI within 14 days of stopping BRISDELLE unless directed to do so by your healthcare provider.
  - Do not start BRISDELLE if you stopped taking an MAOI in the last 14 days unless directed to do so by your healthcare provider.
  - People who take BRISDELLE close in time to an MAOI may have a serious or life-threatening side effect called serotonin syndrome. Get medical help right away if you have any of these symptoms:
    - high fever
    - uncontrolled muscle spasms
    - stiff muscles
    - rapid changes in heart rate or blood pressure
    - confusion
    - loss of consciousness (pass out)
    - nausea, vomiting, or diarrhea

- take thioridazine. Do not take thioridazine together with BRISDELLE because this can cause serious heart rhythm problems or sudden death.
- take the antipsychotic medicine pimozide. Do not take pimozide together with BRISDELLE because this can cause serious heart problems.
- are allergic to paroxetine or any of the ingredients in BRISDELLE. See the end of this Medication Guide for a complete list of ingredients in BRISDELLE.
- are pregnant or become pregnant. BRISDELLE can harm your unborn baby. Call your healthcare provider if you become pregnant while taking BRISDELLE.

What should I tell my healthcare provider before taking BRISDELLE?

Before taking BRISDELLE, tell your healthcare provider about all of your medical conditions, including if you:

- have liver problems
- have kidney problems
- have or had seizures or convulsions
- have or have a family history of bipolar disorder, mania or hypomania
- have low sodium levels in your blood
- have or had bleeding problems
- have glaucoma (high pressure in the eye)
- have bone problems

Tell your healthcare provider about all the medicines that you take, including prescription and over-the-counter medicines, vitamins, and herbal supplements. BRISDELLE and some medicines may interact with each other, may not work as well, or may cause serious side effects when taken together.

If you take BRISDELLE, you should not take any other medicines that contain paroxetine, including Paxil, Paxil CR and Pexeva.

Especially tell your healthcare provider if you take:

- triptans used to treat migraine headache
- medicines used to treat mood, anxiety, psychotic or thought disorders, including MAOIs, SSRIs, tricyclics, lithium, buspirone, or antipsychotics
- tramadol, fentanyl, meperidine, methadone, or other opioids
- over-the-counter supplements such as tryptophan or St. John’s Wort
- amphetamines
- thioridazine
- pimozide
- tamoxifen
- atomoxetine
- cimetidine
- digoxin
- theophylline
- medicines to treat irregular heart rate (like propafenone, flecainide, and encainide)
- medicines used to treat schizophrenia
- certain medicines used to treat HIV infection
- the blood thinner warfarin
- nonsteroidal anti-inflammatory drugs (NSAIDs) (like ibuprofen, naproxen, or aspirin)
- certain medicines used to treat seizures (like phenobarbital and phenytoin)
- other drugs containing paroxetine, the medicine in BRISDELLE

Ask your healthcare provider if you are not sure if you are taking any of these medications.

Your healthcare provider or pharmacist can tell you if it is safe to take BRISDELLE with your other medicines. Do not start or stop any medicine while taking BRISDELLE without talking to your healthcare provider first.

How should I take BRISDELLE?

- Take BRISDELLE exactly as your healthcare provider tells you to take it.
- Take BRISDELLE 1 time each day at bedtime.
- BRISDELLE may be taken with or without food.
- If you take too much BRISDELLE, call your healthcare provider or Poison Help line right away, or go to the nearest emergency room right away.

What are the possible side effects of BRISDELLE?

BRISDELLE may cause serious side effects, including:

- See “What is the most important information I should know about BRISDELLE?”
- Serotonin syndrome. This condition can be life-threatening and can happen when you take BRISDELLE with certain other medicines. Call your healthcare provider or go to the nearest hospital emergency room right away if you have any of the following symptoms of serotonin syndrome:
  - agitation (nervousness), hallucinations, coma or other changes in mental status
  - coordination problems or muscle twitching (small movements of the muscles that you cannot control)
  - racing heartbeat, high or low blood pressure
  - sweating or fever
  - nausea, vomiting, or diarrhea
  - muscle rigidity
  - dizziness
  - flushing
  - tremors
  - seizures

- Reduced effectiveness of tamoxifen. Tamoxifen (a medicine used to treat breast cancer) may not work as well if it is taken while you take BRISDELLE. If you are taking tamoxifen, tell your healthcare provider before starting BRISDELLE.
- Abnormal bleeding. BRISDELLE may increase your risk of bleeding or bruising, especially if you take the blood thinner warfarin or non-steroidal anti-inflammatory drugs (NSAIDs) like ibuprofen, naproxen, or aspirin.
- Visual problems (angle-closure glaucoma). BRISDELLE may cause a visual problem called angle-closure glaucoma. Symptoms may include:
  - eye pain
  - changes in vision
  - swelling or redness in or around the eye

Only some people are at risk for these problems. You may want to undergo an eye examination to see if you are at risk and receive preventative treatment if you are.

- Low salt (sodium) levels in the blood. Elderly people and those taking diuretics or are dehydrated are at greater risk of experiencing low salt levels in their blood. Symptoms may include:
  - headache
  - weakness or feeling unsteady
  - confusion, problems concentrating or thinking or memory problems
  - seeing or hearing things that are not there (hallucinations)
  - fainting (syncope)
  - seizures
  - stopping breathing (respiratory arrest)

- Bone fractures. Women who take BRISDELLE may have a higher risk of bone fractures. Contact your healthcare provider if you have pain in a bone.
- Manic episodes. Manic episodes may happen in people with bipolar disorder who take BRISDELLE. Symptoms may include:
  - greatly increased energy
  - severe trouble sleeping
  - racing thoughts
  - reckless behavior
  - unusually grand ideas
  - excessive happiness or irritability
  - talking more or faster than usual

- Seizures
- Sexual problems (dysfunction). Taking selective serotonin reuptake inhibitors (SSRIs), including BRISDELLE, may cause symptoms of sexual problems. Symptoms in females may include:
  - decreased sexual drive
  - delayed or inability to have an orgasm

The most common side effects of BRISDELLE include:

- headache
- tiredness
- nausea and vomiting

Tell your healthcare provider if you have any side effect that bothers you or does not go away. These are not all the possible side effects of BRISDELLE. For more information, ask your healthcare provider or pharmacist.

Call your doctor for medical advice about side effects. You may report side effects to FDA at 1-800-FDA-1088

How should I store BRISDELLE?

- Store BRISDELLE at room temperature between 68°F to 77°F (20°C to 25°C).
- Keep BRISDELLE out of the light.
- Keep BRISDELLE dry.

Keep BRISDELLE and all medicines out of the reach of children

General information about the safe and effective use of BRISDELLE.

Medicines are sometimes prescribed for purposes other than those listed in a Medication Guide. Do not use BRISDELLE for a condition for which it was not prescribed. Do not give BRISDELLE to other people, even if they have the same condition. It may harm them. You may ask your healthcare provider or pharmacist for information about BRISDELLE that is written for healthcare professionals.

What are the ingredients in BRISDELLE?

Active ingredient: paroxetine

Inactive ingredients: dibasic calcium phosphate, sodium starch glycolate, magnesium stearate, gelatin, titanium dioxide, FD&C Yellow #6, FD&C Red #3, FD&C Red #40, shellac and black iron oxide.

Manufactured for:

Legacy Pharma Inc., George Town, Grand Cayman

BRISDELLE is a registered trademark of Legacy Pharma Inc.

©2025 Legacy Pharma Inc. All rights reserved.

For more information about BRISDELLE go to www.BRISDELLE.com

MDG90757001

This Medication Guide has been approved by the U.S. Food and Drug Administration Revised: 02/2025

PRINCIPAL DISPLAY PANEL

BRISDELLE (paroxetine) Capsules is available as 7.5 mg - NDC 83107-027-30 - 30 Caps Blister Label

BRISDELLE (paroxetine) Capsules is available as 7.5 mg - NDC 83107-027-30 - 30 Caps Blister Carton